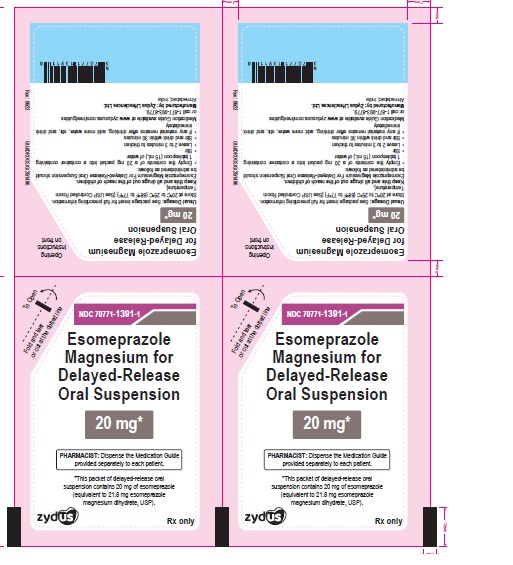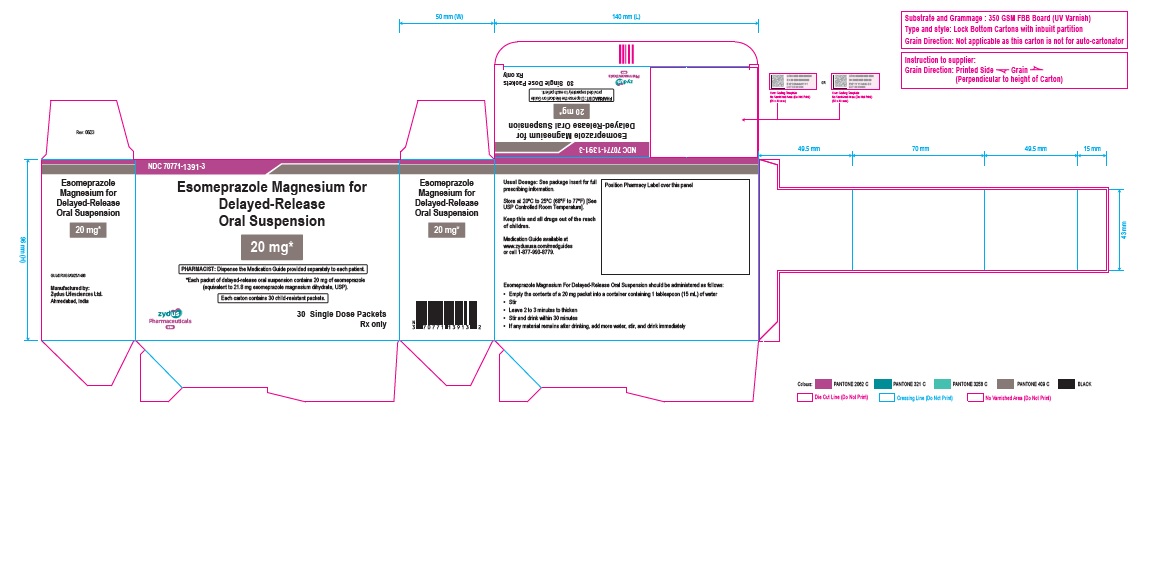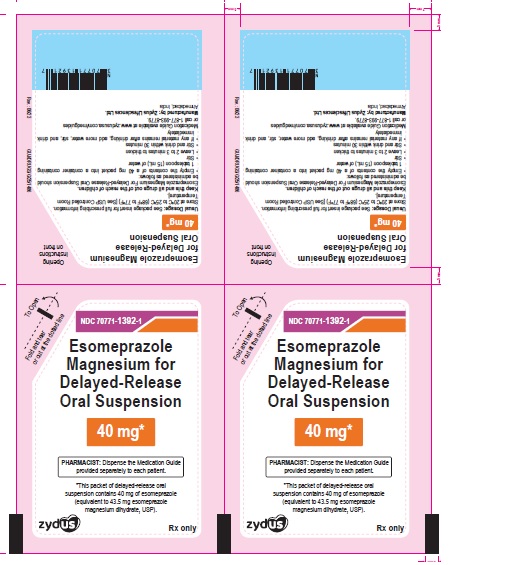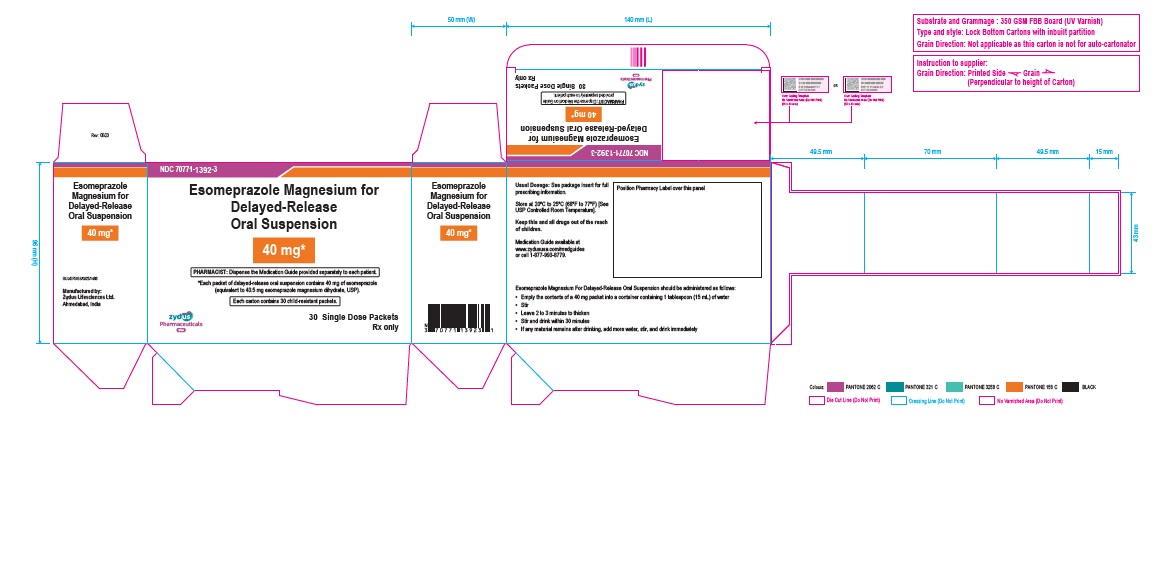 DRUG LABEL: Esomeprazole Magnesium
NDC: 70771-1391 | Form: GRANULE, DELAYED RELEASE
Manufacturer: Zydus Lifesciences Limited
Category: prescription | Type: HUMAN PRESCRIPTION DRUG LABEL
Date: 20241128

ACTIVE INGREDIENTS: ESOMEPRAZOLE MAGNESIUM DIHYDRATE 20 mg/1 1
INACTIVE INGREDIENTS: ANHYDROUS CITRIC ACID; CROSPOVIDONE; DEXTROSE; FERRIC OXIDE RED; GLYCERYL MONOSTEARATE; HYDROXYPROPYL CELLULOSE (90000 WAMW); MAGNESIUM STEARATE; MANNITOL; METHACRYLIC ACID AND ETHYL ACRYLATE COPOLYMER; POLYSORBATE 80; POVIDONE; STRAWBERRY; SUCROSE; TALC; TRIETHYL CITRATE; XANTHAN GUM

ESOMEPRAZOLE MAGNESIUM for delayed-release oral suspension

PACKAGE LABEL.PRINCIPAL DISPLAY PANEL

Esomeprazole Magnesium For Delayed-Release Oral Suspension

NDC 70771-1391-1

20 mg packet

Rx Only

Esomeprazole Magnesium For Delayed-Release Oral Suspension

NDC 70771-1391-3 unit dose packages of 30: 20 mg packets

Rx Only

Esomeprazole Magnesium For Delayed-Release Oral Suspension

NDC 70771-1392-1

40 mg packet

Rx Only

Esomeprazole Magnesium For Delayed-Release Oral Suspension

NDC 70771-1392-3 unit dose packages of 30: 40 mg packets

Rx Only